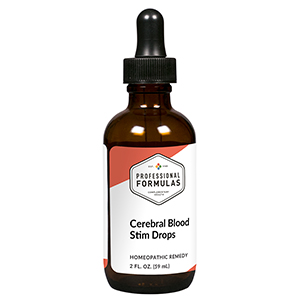 DRUG LABEL: Cerebral Blood Stim Drops
NDC: 63083-2086 | Form: LIQUID
Manufacturer: Professional Complementary Health Formulas
Category: homeopathic | Type: HUMAN OTC DRUG LABEL
Date: 20190815

ACTIVE INGREDIENTS: GINKGO 3 [hp_X]/59 mL; SCUTELLARIA LATERIFLORA WHOLE 3 [hp_X]/59 mL; CONVALLARIA MAJALIS 4 [hp_X]/59 mL; ACONITUM NAPELLUS WHOLE 6 [hp_X]/59 mL; BOS TAURUS BRAIN 6 [hp_X]/59 mL; PHOSPHORUS 6 [hp_X]/59 mL; THYROID, UNSPECIFIED 6 [hp_X]/59 mL; HUMAN HERPESVIRUS 1 12 [hp_X]/59 mL; HYDROGEN CYANIDE 30 [hp_X]/59 mL
INACTIVE INGREDIENTS: ALCOHOL; WATER

C86

ACTIVE INGREDIENTS

Ginkgo biloba 3X
Scutellaria lateriflora 3X
Convallaria majalis 4X, 6X, 12X, 30X
Aconitum napellus 6X
Brain 6X
Phosphorus 6X
Thyroid 6X
Variolinum 12X
Hydrocyanicum acidum 30X

QUESTIONS

Professional Formulas

PO Box 2034 Lake Oswego, OR 97035

INDICATIONS

For the temporary relief of occasional headache, dizziness, or confusion.*

PURPOSE

*Claims based on traditional homeopathic practice, not accepted medical evidence. Not FDA evaluated.

WARNINGS

Consult a doctor if condition worsens or if symptoms persist. Keep out of the reach of children. In case of overdose, get medical help or contact a poison control center right away. If pregnant or breastfeeding, ask a healthcare professional before use.

Keep out of the reach of children.

PREGNANCY OR BREAST FEEDING

If pregnant or breastfeeding, ask a healthcare professional before use.

DIRECTIONS

Place drops under tongue 30 minutes before/after meals. Adults and children 12 years and over: Take 10 drops up to 3 times per day. Consult a physician for use in children under 12 years of age.

OTHER INFORMATION

Tamper resistant. If seal is broken, do not use. After opening, close container tightly and store at room temperature away from heat.

INACTIVE INGREDIENTS

20% ethanol, purified water.

LABEL

Est 1985

Professional Formulas

Complementary Health

Cerebral Blood Stim Drops

Homeopathic Remedy

2 FL. OZ. (59 mL)